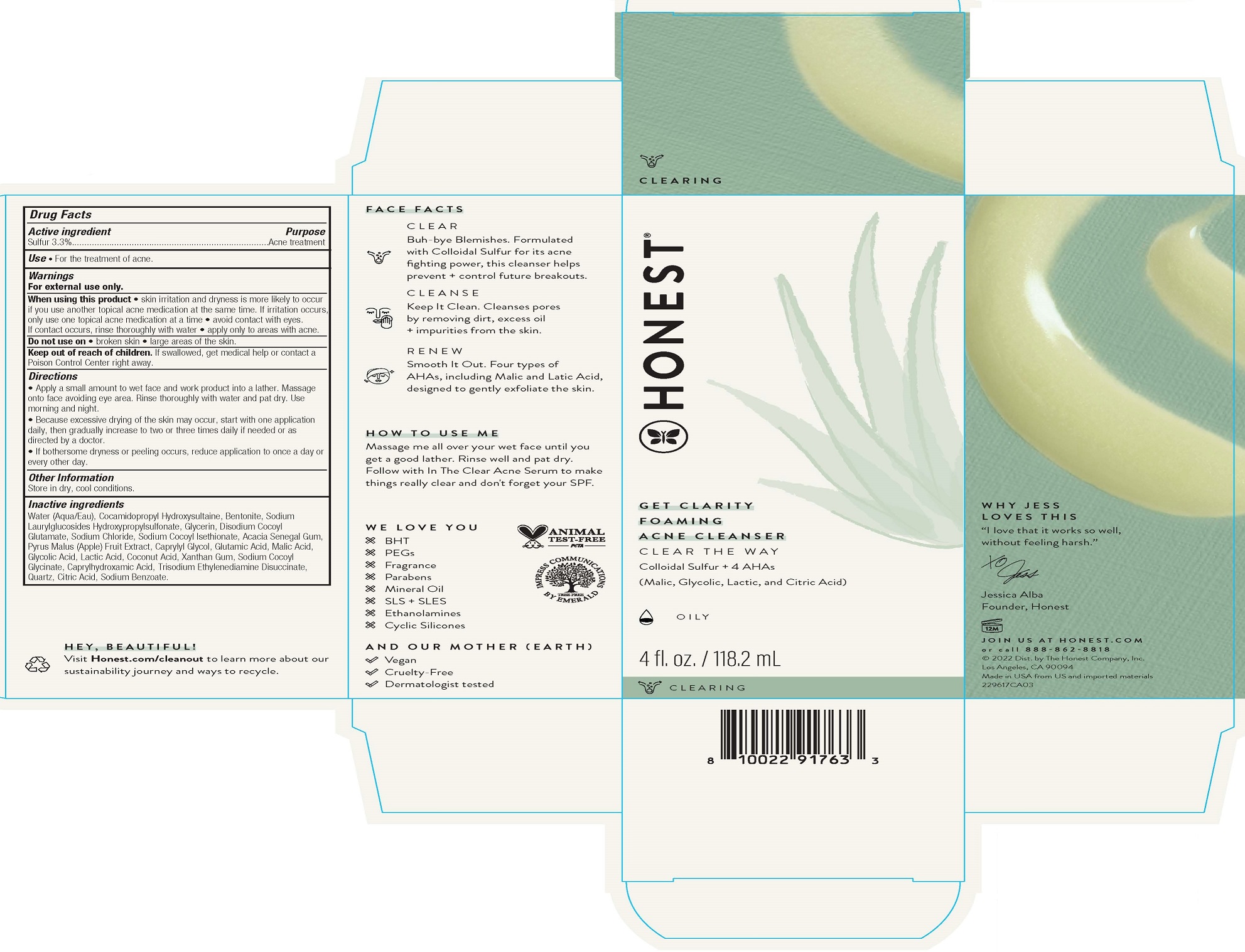 DRUG LABEL: Get Clarity Foaming Acne Cleanser
NDC: 69366-413 | Form: CREAM
Manufacturer: The Honest Company, Inc
Category: otc | Type: HUMAN OTC DRUG LABEL
Date: 20231219

ACTIVE INGREDIENTS: SULFUR 3.3 g/100 mL
INACTIVE INGREDIENTS: LACTIC ACID; SODIUM COCOYL GLYCINATE; SODIUM BENZOATE; WATER; COCAMIDOPROPYL HYDROXYSULTAINE; BENTONITE; SODIUM LAURYLGLUCOSIDES HYDROXYPROPYLSULFONATE; GLYCERIN; DISODIUM COCOYL GLUTAMATE; MALIC ACID, L-; SODIUM CHLORIDE; ACACIA; APPLE; XANTHAN GUM; TRISODIUM ETHYLENEDIAMINE DISUCCINATE; SILICON DIOXIDE; GLUTAMIC ACID; CAPRYLYL GLYCOL; CAPRYLHYDROXAMIC ACID; SODIUM COCOYL ISETHIONATE; COCONUT ACID; ANHYDROUS CITRIC ACID; GLYCOLIC ACID

Get Clarity Foaming Acne Cleanser

Active ingredientSulfur 3.3%

PURPOSE

PurposeAcne treatment

INDICATIONS AND USAGE

Use• For the treatment of acne.

Warnings

For external use only.

When using this product• skin irritation and dryness is more likely to occur if you use another topical acne medication at the same time. If irritation occurs, only use one topical acne medication at a time • avoid contact with eyes. If contact occurs, rinse thoroughly with water • apply only to areas with acne.

Do not use on• broken skin • large areas of the skin

Keep out of reach of children. If swallowed, get medical help or contact a Poison Control Center right away.

Directions

• Apply a small amount to wet face and work product into a lather. Massage onto face avoiding eye area. Rinse thoroughly with water and pat dry. Use morning and night.

• Because excessive drying of the skin may occur, start with one application daily, then gradually increase to two or three times daily if needed or as directed by a doctor.

• If bothersome dryness or peeling occurs, reduce application to once a day or every other day.

Other informationStore in dry, cool conditions.

Inactive ingredients

Water (Aqua/Eau), Cocamidopropyl Hydroxysultaine, Bentonite, Sodium Laurylglucosides Hydroxypropylsulfonate, Glycerin, Disodium Cocoyl Glutamate, Sodium Chloride, Sodium Cocoyl Isethionate, Acacia Senegal Gum, Pyrus Malus (Apple) Fruit Extract, Caprylyl Glycol, Glutamic Acid, Malic Acid, Glycolic Acid, Lactic Acid, Coconut Acid, Xanthan Gum, Sodium Cocoyl Glycinate, Caprylhydroxamic Acid, Trisodium Ethylenediamine Disuccinate, Quartz, Citric Acid, Sodium Benzoate.

HOW TO USE ME

Massage me all over your wet face until you get a good lather. Rinse well and pat dry. Follow with In The Clear Acne Serum to make things really clear and don't forget your SPF.

PACKAGE LABEL

HONEST®

GET CLARITY FOAMING ACNE CLEANSER

CLEAR THE WAY

Colloidal Sulfer + 4 AHAs

(Malic, Glycolic, Lactic and Citric Acid)

OILY

4 fl. oz. / 118.2 mL

888-862-8818

©2022 Dist. by The Honest Company, Inc.

Los Angeles, CA 90094

Made in USA from US and imported materials